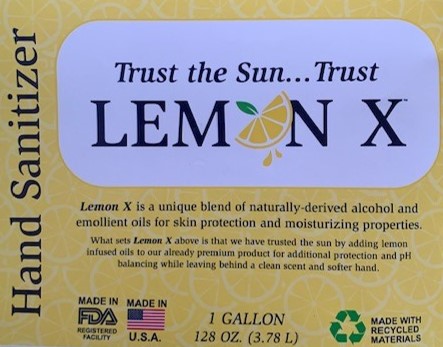 DRUG LABEL: LEMON X Hand Sanitizer
NDC: 77584-103 | Form: GEL
Manufacturer: DCI Binzel Chemical Laboratories
Category: otc | Type: HUMAN OTC DRUG LABEL
Date: 20211231

ACTIVE INGREDIENTS: ALCOHOL 73 mL/100 mL
INACTIVE INGREDIENTS: FD&C YELLOW NO. 5 0.5 mL/100 mL; WATER 22 mL/100 mL; GLYCERIN 1.5 mL/100 mL; FRAGRANCE LEMON ORC2001060 0.5 mL/100 mL; DENATONIUM BENZOATE 0.0001 mL/100 mL; ALPHA-TOCOPHEROL 1.5 mL/100 mL; CARBOMER HOMOPOLYMER TYPE A 0.75 mL/100 mL; TRIETHANOLAMINE 2-CYCLOHEXYL-4,6-DINITROPHENOLATE 0.25 mL/100 mL

LEMON X

Drug Facts

Active Ingredient(s)

Ethyl Alcohol 73% v/v. Purpose: Antiseptic

PURPOSE

Antiseptic, Hand Sanitizer

Use

Hand Sanitizer to help reduce bacteria on the skin.

Recommended for repeated use.

Warnings

For external use only. Flammable. Keep away from fire or flame.

Do not use

- When using this product do not use in or near the eyes.
- In case of contact, rinse eyes thouroughly with water.

WHEN USING

Do not drink. Not edible. In case of accidental ingestion, seek professional assistance or contact a Poison Control Center immediately.

STOP USE

Discontinue use if irritation or redness develops. If condition persistes for more than 72 hours, consult a doctor.

Keep out of reach of children. Children should only use this product under adult supervision.

Directions

- Place enough product in your palm to thoroughly spread on both hands and rub into the skin until dry.
- Recommended for repeated use.

Other information

- Do not store above 105F.
- May discolor some fabrics.
- Harmful to wood finishes and plastics.

Inactive Ingredients

Deionized water, Glycerin, Carbomer, Triethanolamine, Fragrance, Vitamin E (Tocopheryl Acetate), FD&C Yellow No. 6

Package Label - Principal Display Panel

1 Gallon 128 oz. (3.78L) NDC: 77584-103-01